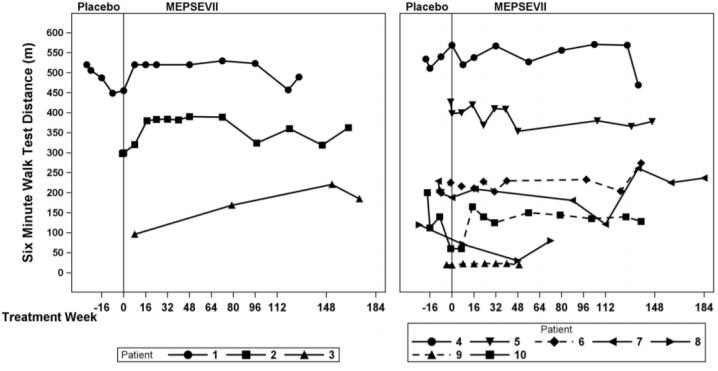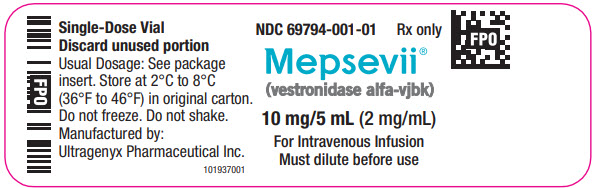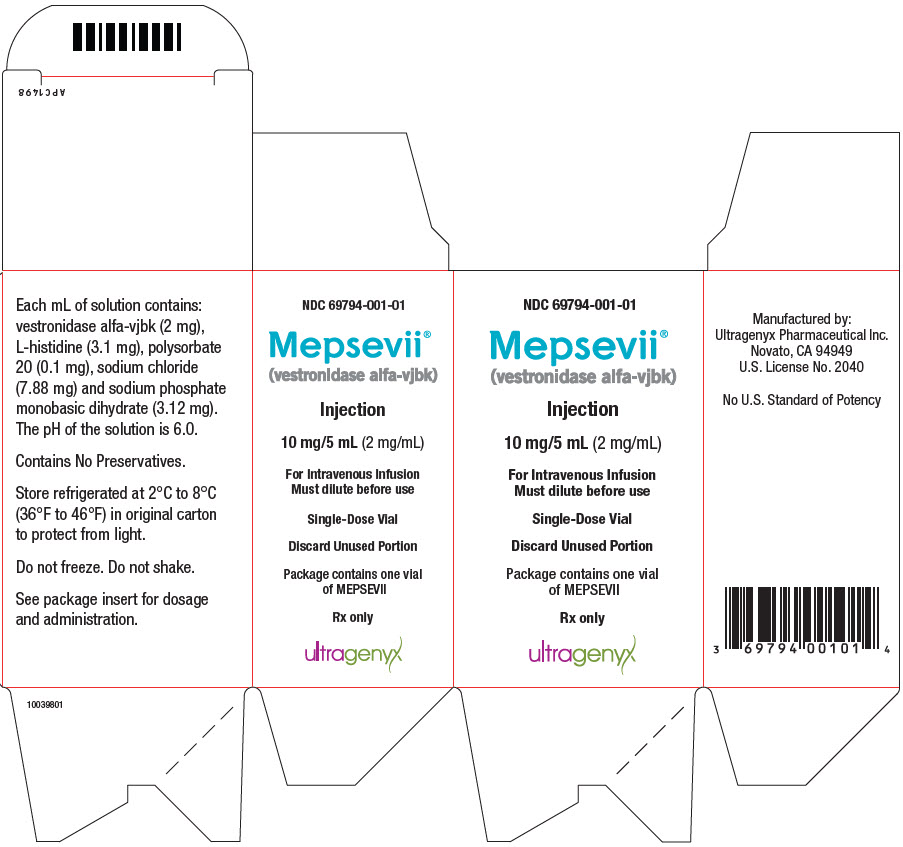 DRUG LABEL: MEPSEVII
NDC: 69794-001 | Form: INJECTION
Manufacturer: Ultragenyx Pharmaceutical Inc.
Category: prescription | Type: HUMAN PRESCRIPTION DRUG LABEL
Date: 20251118

ACTIVE INGREDIENTS: VESTRONIDASE ALFA 2 mg/1 mL
INACTIVE INGREDIENTS: SODIUM PHOSPHATE, MONOBASIC, DIHYDRATE 3.12 mg/1 mL; SODIUM CHLORIDE 7.88 mg/1 mL; HISTIDINE 3.1 mg/1 mL; POLYSORBATE 20 0.1 mg/1 mL

HIGHLIGHTS OF PRESCRIBING INFORMATION

These highlights do not include all the information needed to use MEPSEVII safely and effectively. See full prescribing information for MEPSEVII.
MEPSEVII® (vestronidase alfa-vjbk) injection, for intravenous use
Initial U.S. Approval: 2017

WARNING: ANAPHYLAXIS

See full prescribing information for complete boxed warning.

- Anaphylaxis has occurred with MEPSEVII administration, as early as the first dose (5.1), therefore appropriate medical support should be readily available when MEPSEVII is administered.
- Closely observe patients during and for 60 minutes after MEPSEVII infusion (2.2, 5.1).
- Immediately discontinue the MEPSEVII infusion if the patient experiences anaphylaxis (2.2, 5.1).

1 INDICATIONS AND USAGE

MEPSEVII is a recombinant human lysosomal beta glucuronidase indicated in pediatric and adult patients for the treatment of Mucopolysaccharidosis VII (MPS VII, Sly syndrome).

Limitations of Use

The effect of MEPSEVII on the central nervous system manifestations of MPS VII has not been determined. (1)

2 DOSAGE AND ADMINISTRATION

- The recommended dosage is 4 mg/kg administered every two weeks as an intravenous infusion. (2.1)
- Premedication with a non-sedating antihistamine with or without an anti-pyretic is recommended 30 to 60 minutes prior to the start of the infusion. (2.2, 5.1)
- Administer the infusion over approximately 4 hours. In the first hour of infusion, infuse 2.5% of the total volume. After the first hour, the rate can be increased to infuse the remainder of the volume over 3 hours as tolerated. See Table 1 in the full prescribing information for the rate of infusion by dose and body weight. (2.4)
- For additional information on preparation, administration, and storage see the full prescribing information. (2.3, 2.4)

3 DOSAGE FORMS AND STRENGTHS

Injection: 10 mg/5 mL (2 mg/mL) in a single-dose vial (3)

4 CONTRAINDICATIONS

None (4)

6 ADVERSE REACTIONS

Most common adverse reactions (≥1 patient) are: Infusion site extravasation, diarrhea, rash, anaphylaxis, infusion site swelling, peripheral swelling and pruritus. (6.1)

To report SUSPECTED ADVERSE REACTIONS, contact Ultragenyx at 1-888-756-8657 or FDA at 1-800-FDA-1088 or www.fda.gov/medwatch.

FULL PRESCRIBING INFORMATION

WARNING: ANAPHYLAXIS

- Anaphylaxis has occurred with MEPSEVII administration, as early as the first dose [see Warnings and Precautions (5.1)], therefore appropriate medical support should be readily available when MEPSEVII is administered.
- Closely observe patients during and for 60 minutes after MEPSEVII infusion [see Dosage and Administration (2.2), Warnings and Precautions (5.1)].
- Immediately discontinue the MEPSEVII infusion if the patient experiences anaphylaxis [see Dosage and Administration (2.2), Warnings and Precautions (5.1)].

1 INDICATIONS AND USAGE

MEPSEVII is indicated in pediatric and adult patients for the treatment of Mucopolysaccharidosis VII (MPS VII, Sly syndrome).

Limitations of Use

The effect of MEPSEVII on the central nervous system manifestations of MPS VII has not been determined.

2 DOSAGE AND ADMINISTRATION

2.1 Recommended Dosage

MEPSEVII should be administered under the supervision of a healthcare professional with the capability to manage anaphylaxis. Premedication is recommended 30 to 60 minutes prior to the start of the infusion [see Dosage and Administration (2.2)].

The recommended dosage of MEPSEVII is 4 mg/kg administered by intravenous infusion every two weeks.

Administer the infusion over approximately 4 hours. Infuse the first 2.5% of the total volume over the first hour. After the first hour, increase the infusion rate as tolerated in order to complete infusion over the following 3 hours according to the recommended rate guidelines in Table 1 [see Dosage and Administration (2.4)].

2.2 Premedication

- Administration of a non-sedating antihistamine with or without an anti-pyretic medication is recommended 30 to 60 minutes prior to the start of the infusion for patient comfort.
- Follow the instructions in Table 1 for the rate of MEPSEVII infusion [see Dosage and Administration (2.4)].
- Observe patients closely during the infusion and following the infusion for a minimum of 60 minutes for the development of anaphylaxis [see Warnings and Precautions (5.1)].
- Discontinue the infusion immediately if the patient experiences a severe systemic reaction, including anaphylaxis [see Warnings and Precautions (5.1)].

2.3 Preparation Instructions

Prepare MEPSEVII according to the following steps using aseptic technique:

1. Determine the number of vials to be diluted based on the patient's actual weight and the recommended dose of 4 mg/kg, using the following calculations (a-b):

a. Total dose (mg) = Patient's weight (kg) x 4 mg/kg (recommended dose)

b. Total number of vials = Total dose (mg) divided by 10 mg/vial

2. Round to the next whole vial and remove the required number of vials from the refrigerator to allow them to reach room temperature. Do not heat, microwave or shake vials.

a. Volume (mL) of calculated dose = Total dose (mg) divided by the 2 mg/mL concentration

3. The final solution will be a 1:1 dilution of MEPSEVII with 0.9% Sodium Chloride Injection, USP. More than 1:1 dilution may be used if the patient can tolerate additional infusion volume, taking into consideration cardiac function and fluid status.

4. For a 1:1 dilution, prepare the solution at room temperature, as follows:

a. Select an empty infusion bag, sized upon the total volume of the final solution.

b. Prior to withdrawing MEPSEVII from the vial, visually inspect the solution for particulate matter and discoloration. Because this is a protein solution, slight flocculation (thin translucent fibers) may occur. The MEPSEVII solution should be colorless to slightly yellow. Discard if the solution is discolored or if there is particulate matter in the solution.

c. Slowly withdraw the volume of the calculated MEPSEVII dose from the appropriate number of vials (step 2a) using caution to avoid excessive agitation and any air or frothing. Use a sufficiently large needle (18 gauge) to minimize bubbles in the solution.

d. Slowly add MEPSEVII to the infusion bag using care to avoid agitation, ensuring liquid to liquid contact without generating bubbles or turbulence.

e. Add 0.9% Sodium Chloride Injection, USP equal to the volume of MEPSEVII to the infusion bag.

f. Gently rock the infusion bag to ensure proper distribution of MEPSEVII. Do not shake the solution.

2.4 Administration Instructions

Administer MEPSEVII as follows:

1. The rate of infusion: In the first hour infuse 2.5% of the total volume, and infuse the remaining volume over the subsequent three hours (see Table 1). Account for any dead space in the lines to ensure 2.5% of the total infusion volume is delivered into the patient's bloodstream during the first hour of infusion.
2. Use an infusion set equipped with an in-line, low-protein binding 0.2 micron filter to administer the diluted MEPSEVII solution.
3. Do not flush the line containing MEPSEVII to avoid a rapid bolus of infused enzyme. Due to the low infusion rate, additional saline may be added through a separate line (piggyback or Y tube) to maintain sufficient intravenous flow to prevent clotting or line blockage.
4. Do not infuse with other products in the infusion tubing. Compatibility with other products has not been evaluated.
5. Use MEPSEVII immediately after dilution and complete the infusion within 42 hours from the time of dilution. Discard any unused product.

Stability

If immediate use is not possible, the diluted solution may be stored up to 36 hours under refrigeration at 2°C to 8°C (36°F to 46°F) followed by up to 6 hours at room temperature up to a maximum of 25°C (77°F).

Table 1. Recommended Infusion Rate Schedule by Patient Weight for Administration of MEPSEVII at Recommended Dose of 4 mg/kg
Patient Weight Range (kg) | Total MEPSEVII Dose Range (mg) | Total MEPSEVII Volume (rounded) (mL) | Total Infusion Volume of Drug and diluent (infused over 4 hours) (mL) | Infusion Rate for 1 st Hour (2.5%) (mL/h) | Infusion Rate per Hour for Subsequent 3 Hours (97.5%/3) (mL/h)
3.5-5.9 | 14-23.6 | 10 | 20 | 0.5 | 6.5
6-8.4 | 24-33.6 | 15 | 30 | 0.8 | 9.8
8.5-10.9 | 34-43.6 | 20 | 40 | 1 | 13
11-13.4 | 44-53.6 | 25 | 50 | 1.3 | 16.3
13.5-15.9 | 54-63.6 | 30 | 60 | 1.5 | 19.5
16-18.4 | 64-73.6 | 35 | 70 | 1.8 | 22.8
18.5-20.9 | 74-83.6 | 40 | 80 | 2 | 26
21-23.4 | 84-93.6 | 45 | 90 | 2.3 | 29.3
23.5-25.9 | 94-103.6 | 50 | 100 | 2.5 | 32.5
26-28.4 | 104-113.6 | 55 | 110 | 2.8 | 35.8
28.5-30.9 | 114-123.6 | 60 | 120 | 3 | 39
31-33.4 | 124-133.6 | 65 | 130 | 3.3 | 42.3
33.5-35.9 | 134-143.6 | 70 | 140 | 3.5 | 45.5
36-38.4 | 144-153.6 | 75 | 150 | 3.8 | 48.8
38.5-40.9 | 154-163.6 | 80 | 160 | 4 | 52
41-43.4 | 164-173.6 | 85 | 170 | 4.3 | 55.3
43.5-45.9 | 174-183.6 | 90 | 180 | 4.5 | 58.5
46-48.4 | 184-193.6 | 95 | 190 | 4.8 | 61.8
48.5-50.9 | 194-203.6 | 100 | 200 | 5 | 65
51-53.4 | 204-213.6 | 105 | 210 | 5.3 | 68.3
53.5-55.9 | 214-223.6 | 110 | 220 | 5.5 | 71.5
56-58.4 | 224-233.6 | 115 | 230 | 5.8 | 74.8
58.5-60.9 | 234-243.6 | 120 | 240 | 6 | 78
61-63.4 | 244-253.6 | 125 | 250 | 6.3 | 81.3
63.5-65.9 | 254-263.6 | 130 | 260 | 6.5 | 84.5
66-68.4 | 264-273.6 | 135 | 270 | 6.8 | 87.8
68.5-70.9 | 274-283.6 | 140 | 280 | 7 | 91

3 DOSAGE FORMS AND STRENGTHS

Injection: 10 mg/5 mL (2 mg/mL) as a colorless to slightly yellow liquid in a single-dose vial.

4 CONTRAINDICATIONS

None.

5 WARNINGS AND PRECAUTIONS

5.1 Anaphylaxis

Anaphylaxis to MEPSEVII was reported in 2 of 20 patients in the clinical program [see Adverse Reactions (6.1)]. These reactions occurred during MEPSEVII infusion and were observed as early as the first dose of MEPSEVII for one patient. Manifestations included respiratory distress, cyanosis, decreased oxygen saturation, and hypotension. The two patients with anaphylaxis to MEPSEVII during the clinical trials had one occurrence each and tolerated subsequent infusions of MEPSEVII, without recurrence.

Anaphylaxis can be life-threatening. MEPSEVII should be administered under the supervision of a healthcare professional with the capability to manage anaphylaxis. Patients should be observed for 60 minutes after MEPSEVII administration. If severe systemic reactions occur, including anaphylaxis, immediately discontinue the MEPSEVII infusion and provide appropriate medical treatment. Prior to discharge, inform patients of the signs and symptoms of anaphylaxis and instruct them to seek immediate medical care if symptoms occur. Consider the risks and benefits of re-administering MEPSEVII following anaphylaxis.

6 ADVERSE REACTIONS

The following serious adverse reactions are described below and elsewhere in the labeling:

- Anaphylaxis [see Warnings and Precautions (5.1)]

6.1 Clinical Trials Experience

Because clinical trials are conducted under widely varying conditions, adverse reaction rates observed in the clinical trials of a drug cannot be directly compared to rates in the clinical trials of another drug and may not reflect the rates observed in practice.

The MEPSEVII clinical program included 23 patients aged 5 months to 25 years who received treatment with MEPSEVII at doses up to 4 mg/kg once every two weeks for up to 187 weeks. Nineteen patients were younger than 18 years of age.

Table 2 summarizes the adverse reactions that occurred in Study 301, a randomized start trial in 12 patients with MPS VII between the ages of 8 and 25 years [see Clinical Studies (14)].

Adverse reactions in Table 2 occurred in one or more patients treated with MEPSEVII at a dosage of 4 mg/kg at a higher patient frequency than placebo. Adverse reaction incidence rates are presented in the table below to account for the different duration of exposure to active treatment vs. placebo.

Table 2. Adverse Reactions in Patients with MPS VII in Study 301
Adverse Reaction | MEPSEVII N =12 n (Incidence Rate*) | Placebo N=9 n (Incidence Rate*)
Infusion site extravasation | 4 (0.5) | 1 (0.4)
Diarrhea | 3 (0.4) | 0 (0.0)
Rash | 3 (0.4) | 2 (0.7)
Anaphylaxis | 2 (0.2) | 0 (0.0)
Infusion site swelling | 1 (0.1) | 0 (0.0)
Peripheral swelling | 1 (0.1) | 0 (0.0)
Pruritus | 1 (0.1) | 0 (0.0)

n = number of reactions

*Adverse reaction incidence rates calculated per 8.3 patient years for exposure to MEPSEVII, and 2.7 years of exposure for placebo

Febrile Convulsion

One patient receiving a dose of 4 mg/kg experienced a febrile convulsion during MEPSEVII treatment at Week 66. The infusion was stopped, the patient received anticonvulsants, antipyretics and antibiotics, and the adverse reaction resolved. The patient subsequently was re-challenged without recurrence and continued on treatment.

6.2 Immunogenicity

As with all therapeutic proteins, there is potential for immunogenicity. The detection of antibody formation is highly dependent on the sensitivity and specificity of the assay. Additionally, the observed incidence of antibody (including neutralizing antibody) positivity in an assay may be influenced by several factors including assay methodology, sample handling, timing of sample collection, concomitant medications, and underlying disease. For these reasons, comparison of the incidence of antibodies in the studies described below with the incidence of antibodies in other studies to other vestronidase alfa products may be misleading.

Immunogenicity data were available from 23 patients who received MEPSEVII for up to 187 weeks of treatment. Eighteen out of 23 (78%) patients developed anti-vestronidase alfa-vjbk antibodies (ADA). Ten of the 18 (55.6%) ADA-positive patients were tested positive for neutralizing antibodies (NAb). There is no correlation between ADA titer and NAb development.

Six treatment-naïve patients had pre-existing ADA titers at baseline. ADAs were detected in five of these six patients post-treatment. The post-treatment ADA titers were the same as or below the baseline ADA titer values in two patients, but one of these two patients was positive for NAb. ADA titer values after treatment increased 64-fold, 128-fold, and 364-fold, respectively, in the other three patients.

The presence of ADA titer did not appear to affect reduction in urinary glycosaminoglycans (uGAGs).

8 USE IN SPECIFIC POPULATIONS

8.1 Pregnancy

Risk Summary

There are no available data on MEPSEVII use in pregnant women to determine a drug-associated risk of adverse developmental outcomes. In embryofetal development studies, vestronidase alfa-vjbk administered intravenously to pregnant rats and rabbits during the period of organogenesis showed no adverse developmental outcomes at doses up to 1.6 and 10 times, respectively for rats and rabbits, the exposure at the recommended human dose. In a pre- and post-natal development study in rats, an increased number of stillbirths were observed at exposures less than the recommended human dose (see Data). The clinical relevance of these animal findings is uncertain.

The estimated background risk of major birth defects and miscarriage for the indicated population is unknown. All pregnancies have a background risk of birth defect, loss, or other adverse outcomes. In the U.S. general population, the estimated background risk of major birth defects and miscarriage in clinically recognized pregnancies is 2 to 4% and 15 to 20%, respectively.

Data

Animal Data

In embryofetal development studies, vestronidase alfa-vjbk administered intravenously to pregnant rats (once a week) and rabbits (once every 3 days) during the period of organogenesis showed no adverse developmental outcomes at doses up to 20 mg/kg. The 20 mg/kg dose in rats and rabbits provides approximately 1.6 and 10 times the human exposure (AUC) of 57.9 hr*mcg/mL at the 4 mg/kg dose administered once every other week, respectively.

In a pre- and post-natal developmental study in rats, vestronidase alfa-vjbk was administered every 3 days from gestation day 7 through lactation day 20 at doses of 2 mg/kg, 6 mg/kg, and 20 mg/kg. Mortality and adverse clinical signs were observed in the maternal animals at the 20 mg/kg dose (1.6 times the human exposure (AUC) at the recommended human dose of 4 mg/kg). Subsequently, the 20 mg/kg dose was reduced to 12 mg/kg. Maternal toxicity with mortality in one animal was also observed at the 6 mg/kg dose (0.17 times the AUC at the recommended human dose of 4 mg/kg). At the 2 mg/kg dose (0.01 times the AUC at the recommended human dose of 4 mg/kg), no adverse effects were observed in the maternal animals; however, there was a statistically significant decrease in the number of live births and subsequent increase in the number of stillbirths at this dose.

8.2 Lactation

Risk Summary

There are no data on the presence of vestronidase alfa-vjbk in either human or animal milk, the effects on the breastfed infant, or the effects on milk production. The developmental and health benefits of breastfeeding should be considered along with the mother's clinical need for MEPSEVII and any potential adverse effects on the breastfed infant from vestronidase alfa-vjbk or from the underlying maternal condition.

8.4 Pediatric Use

The safety and effectiveness of MEPSEVII have been established in pediatric patients less than 18 years of age [see Adverse Reactions (6), Clinical Studies (14)].

8.5 Geriatric Use

Clinical trials of MEPSEVII did not include any patients aged 65 and over. It is not known whether elderly patients respond differently from younger patients.

11 DESCRIPTION

Vestronidase alfa-vjbk is a recombinant human lysosomal beta glucuronidase which is a purified human enzyme produced by recombinant DNA technology in a Chinese hamster ovary cell line.

Purified vestronidase alfa-vjbk exists as a homotetramer, with each monomer consisting of 629 amino acids. The calculated isotope average molecular mass of each non-glycosylated peptide chain is 72,562 Da.

The amino acid sequence for vestronidase alfa-vjbk is the same as the amino acid sequence for human beta-glucuronidase (GUS).

MEPSEVII (vestronidase alfa-vjbk) injection for intravenous infusion is a sterile, preservative-free, non-pyrogenic, colorless to slightly yellow liquid supplied in a single-dose vial. Each mL of solution contains vestronidase alfa-vjbk (2 mg), L-histidine (3.1 mg), polysorbate 20 (0.1 mg), sodium chloride (7.88 mg) and sodium phosphate monobasic dihydrate (3.12 mg). The pH of the solution is 6.0.

12 CLINICAL PHARMACOLOGY

12.1 Mechanism of Action

Mucopolysaccharidosis VII (MPS VII or Sly syndrome) is a lysosomal disorder characterized by the deficiency of GUS that results in GAG accumulation in cells throughout the body leading to multisystem tissue and organ damage.

Vestronidase alfa-vjbk is a recombinant form of human GUS and is intended to provide exogenous GUS enzyme for uptake into cellular lysosomes. Mannose-6-phosphate (M6P) residues on the oligosaccharide chains allow binding of the enzyme to cell surface receptors, leading to cellular uptake of the enzyme, targeting to lysosomes and subsequent catabolism of accumulated GAGs in affected tissues.

12.2 Pharmacodynamics

In clinical studies, MEPSEVII treatment resulted in sustained reduction of urinary excretion of GAGs during long-term treatment [see Clinical Studies (14)].

12.3 Pharmacokinetics

The pharmacokinetics of vestronidase alfa-vjbk were evaluated in a total of 23 MPS VII patients including 19 pediatric patients and 4 adults. Serum exposures of vestronidase alfa-vjbk appeared to increase approximately proportionally from 1 mg/kg (0.25 times the approved recommended dosage) to 2 mg/kg (0.5 times the approved recommended dosage), and 4 mg/kg (the recommended dosage). After repeated dosing of 4 mg/kg every other week, the mean ± standard deviation of maximal concentration (Cmax) was 17.3 ± 9.6 mcg/mL (range: 4.7 to 35.7 mcg/mL); and the mean ± standard deviation of area under the concentration-time curve from time zero to the last measurable concentration (AUC0-t) was 50.9 ± 32.2 mcg*hr/mL (range: 17.4 to 153 mcg*hr/mL).

Vestronidase alfa-vjbk concentrations in pediatric patients less than 5 years of age were similar to the concentrations in older children and adults.

Distribution

After repeated dosing of 4 mg/kg every other week in MPS VII patients, the mean ± standard deviation of the total volume of distribution (Vss) was 251 ± 140 mL/kg (range: 97 to 598 mL/kg).

Elimination

After repeated dosing of 4 mg/kg every other week in MPS VII patients, the mean ± standard deviation of the total clearance (CL) was 83.6 ± 43.2 mL/hr/kg (range: 38.3 to 184mL/hr/kg); the mean ± standard deviation of the elimination half-life (t1/2) was 2.33 ± 0.75 hours (range: 0.86 to 3.03 hours). The inter-subject variability (coefficient of variation) in total clearance (CL) was 52%.

Metabolism

Vestronidase alfa-vjbk is a recombinant human enzyme and is therefore eliminated by proteolytic degradation into small peptides and amino acids.

Excretion

No excretion studies have been conducted in humans. Vestronidase alfa-vjbk is not expected to be eliminated through renal or fecal excretion.

13 NONCLINICAL TOXICOLOGY

13.1 Carcinogenesis, Mutagenesis, Impairment of Fertility

Long-term studies in animals to evaluate carcinogenic potential or studies to evaluate the mutagenic potential have not been performed with vestronidase alfa-vjbk.

Vestronidase alfa-vjbk at intravenous doses up to 20 mg/kg administered weekly to rats prior to mating and after mating on gestation days 6, 9, 12, 15 and 18 (females), [approximately up to 4.5 times (male rats) and 1.6 times (female rats) the human AUC0-t of 3440 mcg*min/mL at the 4 mg/kg dose administered once every other week] was found to have no adverse effect on fertility and reproductive performance of male and female rats.

14 CLINICAL STUDIES

The clinical program for MEPSEVII included 23 patients with MPS VII, 17 of whom were evaluable for efficacy, 20 for safety, and 23 for immunogenicity. Patients were enrolled in clinical trials and expanded access protocols receiving treatment at doses up to 4 mg/kg once every two weeks for up to 187 weeks. The patients ranged in age from 5 months to 25 years. Sixteen patients were younger than 18 years of age.

Studies 301 and 202

Study UX003-CL301 (referred to as Study 301, NCT02230566) was a randomized start trial of MEPSEVII 4 mg/kg every two weeks in patients with MPS VII. Twelve patients were randomized to one of four placebo durations before crossing over to active treatment. Three patients received MEPSEVII immediately for a duration of 48 weeks, 3 patients received placebo for 8 weeks then MEPSEVII for 40 weeks, 3 patients received placebo for 16 weeks then MEPSEVII for 32 weeks, and 3 patients received placebo for 24 weeks then MEPSEVII for 24 weeks. Of the 12 patients enrolled in the trial, 4 were male and 8 were female and ranged in age from 8 to 25 years (median 14 years). Nine patients were younger than 18 years of age. The majority of the patients were white (75%), with 50% of Hispanic or Latino ethnicity. Patients who were enrolled in Study 301 were eligible to roll over to Study UX003-CL202 (referred to as Study 202, NCT02432144), an open-label extension trial in which patients received additional doses of MEPSEVII at 4 mg/kg intravenously every other week for up to 144 weeks. Ten patients rolled over directly from the end of Study to Week 0 of Study 202, while 2 patients (17%) had treatment gaps before enrolling in Study 202.

In Study 301, motor function, forced vital capacity, and visual acuity were assessed after 24 weeks of MEPSEVII treatment and measured against pre-specified minimal important differences. The extremely small population of patients with MPS VII globally necessitated the enrollment of all patients able to participate resulting in a highly heterogeneous group. Clinical endpoints were not assessable in some patients due to their extent of disease, age or level of cognition. Repeated assessments of the six minute walk test (6MWT) were feasible in ten of 12 patients and are described further below. Of the three patients who improved on their 6MWT (Figure 1, left panel), two also were noted to have improvement in balance and gross motor proficiency as assessed by the Bruininks-Oseretsky Test of Motor Proficiency (BOT-2).

In this trial, the mean difference in 6MWT distance between MEPSEVII and placebo treatment periods in patients able to perform the test at baseline and subsequent visits through Week 24 is shown in Table 3. The mean difference in 6MWT distance increases with increased treatment duration, however, due to the small size of the trial, standard errors are large.

Table 3. Mean Difference in 6MWT Distance (meters) Between MEPSEVII and Placebo Treatment (Study 301) in Patients with MPS VII
Duration of MEPSEVII Treatment | LS mean 6MWT (meters) (± Standard Error)* | Number and Treatment Assignment of Patients Included in Analyis**
8 weeks | -11 (± 24) | 5 placebo period; 8 MEPSEVII period
16 weeks | 13 (± 32) | 5 placebo period; 8 MEPSEVII period
24 weeks | 18 (± 33) | 5 placebo period; 8 MEPSEVII period

*ANCOVA analysis of change from baseline in least squares (LS) mean between placebo and MEPSEVII for different periods, after adjusting for study cohort, age, and baseline 6MWT distance. Patients who used assistive devices were imputed as zeros in the analysis.

**Number and treatment assignment of patients included in the analysis was based upon a randomized start trial design and patient ability to complete testing. Due to no placebo period for the three patients who received 48 weeks of MEPSEVII in the first cohort of the randomized start design, more data were available for analyses during the treatment period (n=8) than during the placebo period (n=5). While data from 8 participants were available at each time point, due to missing observations, the 8 participants were not the same across all time points.

The observed individual 6MWT distances for the 10 patients who could perform the test in Study 301 and Study 202 through Week 184 are presented in Figure 1. The course of three patients with improvement in distance walked of at least 60 meters during the 301 Study compared to the start of MEPSEVII treatment (Week 0) is shown in the left panel; the relatively stable course in the remaining seven patients, including those who used assistive devices, is shown in the right panel.

Figure 1. 6MWT Distance for MPS VII Patients in Studies 301 and 202

Patient 10 did not use an assistive device at baseline but started using an assistive device post-baseline from Treatment Week 8. Patients 6 and 9 consistently used an assistive device at all visits. A solid line indicates the unassisted assessments and a dotted line indicates the assisted assessments.

Liver and Spleen Volume

In Study 301, imaging by MRI or ultrasound to assess liver and spleen volume was performed in seven of the 12 patients. Most liver volumes were normal or below normal size at baseline (mean 1,591 mL, range 742 to 2,207 mL), and on average were unchanged after treatment (mean 1,459 mL, range 876 to 1,851 mL).

Spleen volumes generally were normal or below normal size at baseline (mean 325 mL, range 131 to 491 mL) and on average were unchanged after treatment (mean 360 mL, range 200 to 582 mL).

Study 203

UX003-CL203 (referred to as Study 203; NCT 02418455) was an open-label, uncontrolled single arm study that enrolled 8 patients less than 5 years of age who received MEPSEVII at a dose of 4 mg/kg every two weeks for 48 weeks of treatment and up to an additional 240 weeks during an optional continuation period. The study evaluated urinary GAG excretion, growth and hepatosplenomegaly. With long-term treatment, urinary GAG levels remained decreased upon exposure to MEPSEVII. At baseline, all 8 patients had impaired growth, and height remained near the 5th percentile relative to age-matched gender norms throughout the trial. No significant changes in hepatosplenomegaly were observed.

Other Investigations

Study UX003-CL201 (referred to as Study 201, NCT01856218) was a single arm, open-label, dose exploration trial completed outside the United States that enrolled three MPS VII patients, ranging in age from 5 years to 25 years. Two patients were male; two patients were white and one was Asian. After 120 weeks of exposure to MEPSEVII, one patient demonstrated a 21% improvement over baseline in forced vital capacity (FVC% predicted) on pulmonary function testing in addition to a 105 meter improvement in the 6MWT. Two other patients with baseline hepatosplenomegaly had reduction in liver volume (24% and 53%) and spleen volume (28% and 47%) after 36 weeks of MEPSEVII treatment.

Expanded access to MEPSEVII treatment was provided to a pediatric patient with MPS VII who required continuous ventilatory support at the start of treatment and was subsequently able to tolerate 9 hours daily off ventilator support after 164 weeks of MEPSEVII treatment.

16 HOW SUPPLIED/STORAGE AND HANDLING

MEPSEVII (vestronidase alfa-vjbk) injection is a colorless to slightly yellow liquid supplied as a carton containing one 10 mg/5 mL (2 mg/mL) single-dose vial (NDC 69794-001-01).

Store under refrigeration at 2°C to 8°C (36°F to 46°F). Do not freeze or shake. Protect from light.

17 PATIENT COUNSELING INFORMATION

Anaphylaxis

Advise patients and caregivers that anaphylaxis has occurred with MEPSEVII administration. Inform patients of the signs and symptoms of anaphylaxis, and have them seek immediate medical care should signs and symptoms occur [see Warnings and Precautions (5.1)].

Manufactured by:
Ultragenyx Pharmaceutical Inc.
Novato, CA 94949
U.S. License No. 2040

PRINCIPAL DISPLAY PANEL - 10 mg/5 mL Vial Label

NDC 69794-001-01
Rx only

Mepsevii®
(vestronidase alfa-vjbk)

10 mg/5 mL (2 mg/mL)

For Intravenous Infusion
Must dilute before use

PRINCIPAL DISPLAY PANEL - 10 mg/5 mL Vial Carton

NDC 69794-001-01

Mepsevii®
(vestronidase alfa-vjbk)

Injection

10 mg/5 mL (2 mg/mL)

For Intravenous Infusion
Must dilute before use

Single-Dose Vial

Discard Unused Portion

Package contains one vial
of MEPSEVII

Rx only

ultragenyx